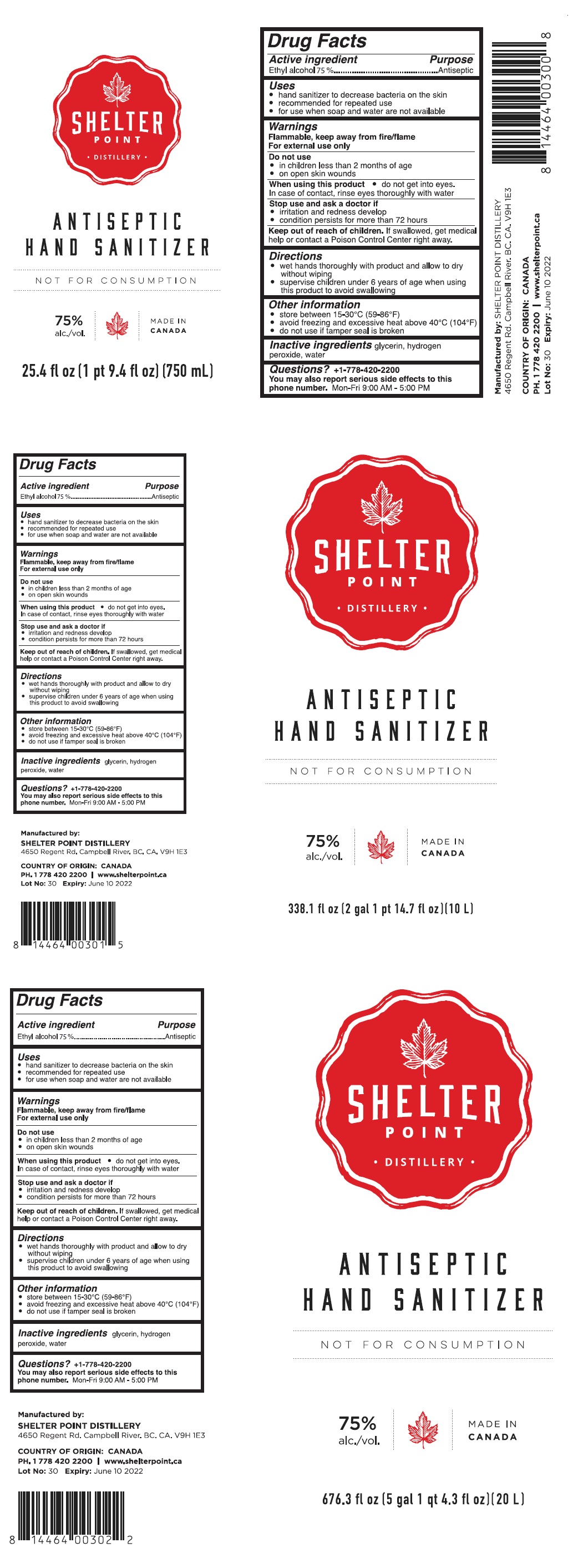 DRUG LABEL: Shelter Point Sanitizer
NDC: 76601-101 | Form: SPRAY
Manufacturer: Shelter Point Distillery Corporation
Category: otc | Type: HUMAN OTC DRUG LABEL
Date: 20200429

ACTIVE INGREDIENTS: ALCOHOL 75 L/100 L
INACTIVE INGREDIENTS: GLYCERIN; HYDROGEN PEROXIDE; WATER

SHELTER POINT DISTILLERY ANTISEPTIC PURPOSE SANITIZER

Active ingredient

Ethyl alcohol 75%

Purpose

Antiseptic

Uses

- hand sanitizer to decrease bacteria on the skin
- recommended for repeated use
- for use when soap and water are not available

Warnings

Flammable, keep away from fire/flame

For external use only

Do not use

- in children less than 2 months of age
- on open skin wounds

When using this product • do not get into eyes. In case of contact, rinse eyes thoroughly with water

Stop use and ask a doctor if

- irritation and redness develop
- condition persists more for more than 72 hours

KEEP OUT OF REACH OF CHILDREN

Keep out of the reach of children. If swallowed, get medical help or contact a Poison Control Center right away.

Directions

- wet hands thoroughly with product and allow to dry without wiping
- supervise children 6 years of age when using this product to avoid swallowing

Other information

- store between 15-30°C (59-86°F)
- avoid freezing and excessive heat above 40°C (104°F)
- do not use if tamper seal is broken

Inactive ingredients glycerin, hydrogen peroxide, water

Questions? +1-778-420-2200

You may also report serious side effects to this phone number.

Mon-Fri 9:00 AM - 5:00 PM

NOT FOR CONSUMPTION

75% alc./vol.

MADE IN CANADA

Manufactured by:

SHELTER POINT DISTILLERY

4650 Regent Rd. Campbell River. BC. CA. V9H 1E3

COUNTRY OF ORIGIN: CANADA

PH. 1 778 420 2200 | www.shelterpont.ca

Expiry: June 10 2022